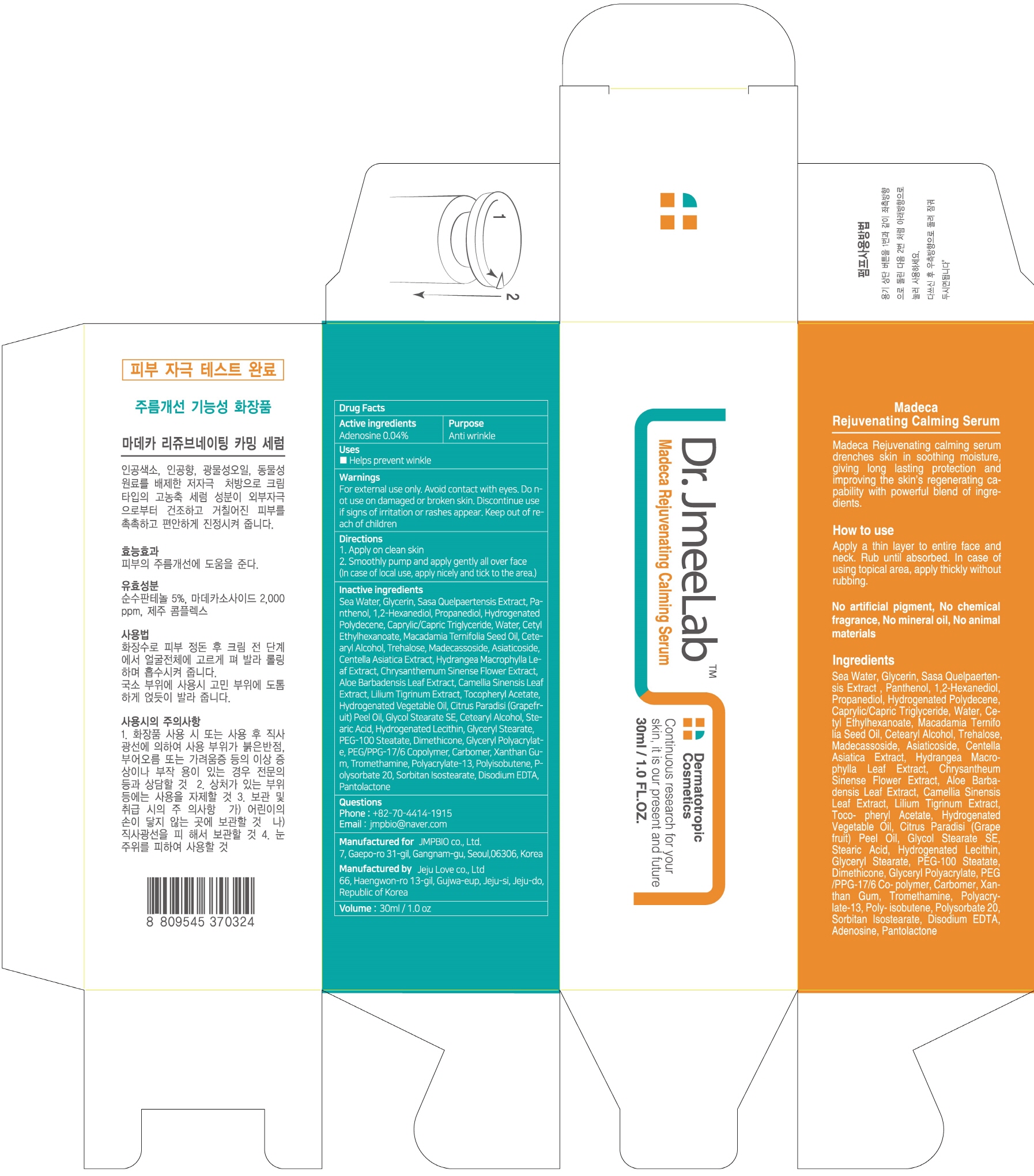 DRUG LABEL: Madeca Rejuvenating Calming Serum
NDC: 72144-010 | Form: CREAM
Manufacturer: JMPBIO co., Ltd.
Category: otc | Type: HUMAN OTC DRUG LABEL
Date: 20190515

ACTIVE INGREDIENTS: Adenosine 0.012 g/30 mL
INACTIVE INGREDIENTS: Water; Glycerin

ACTIVE INGREDIENT

Active ingredients: Adenosine 0.04%

INACTIVE INGREDIENT

Inactive ingredients:

Sea Water, Glycerin, Sasa Quelpaertensis Extract, Panthenol, 1,2-Hexanediol, Propanediol, Hydrogenated Polydecene, Caprylic/Capric Triglyceride, Water, Cetyl Ethylhexanoate, Macadamia Ternifolia Seed Oil, Cetearyl Alcohol, Trehalose, Madecassoside, Asiaticoside, Centella Asiatica Extract, Hydrangea Macrophylla Leaf Extract, Chrysanthemum Sinense Flower Extract, Aloe Barbadensis Leaf Extract, Camellia Sinensis Leaf Extract, Lilium Tigrinum Extract, Tocopheryl Acetate, Hydrogenated Vegetable Oil, Citrus Paradisi (Grapefruit) Peel Oil, Glycol Stearate SE, Cetearyl Alcohol, Stearic Acid, Hydrogenated Lecithin, Glyceryl Stearate, PEG-100 Steatate, Dimethicone, Glyceryl Polyacrylate, PEG/PPG-17/6 Copolymer, Carbomer, Xanthan Gum, Tromethamine, Polyacrylate-13, Polyisobutene, Polysorbate 20, Sorbitan Isostearate, Disodium EDTA, Pantolactone

PURPOSE

Purpose: Anti wrinkle

WARNINGS

For external use only Avoid contact with eyes. Do not use on damaged or broken skin. Discontinue use if signs of irritation or rashes appear. Keep out of reach of children

KEEP OUT OF REACH OF CHILDREN

Uses

- Helps prevent winkle

Directions

1. Apply on clean skin

2. Smoothly pump and apply gently all over face (In case of local use, apply nicely and tick to the area.)